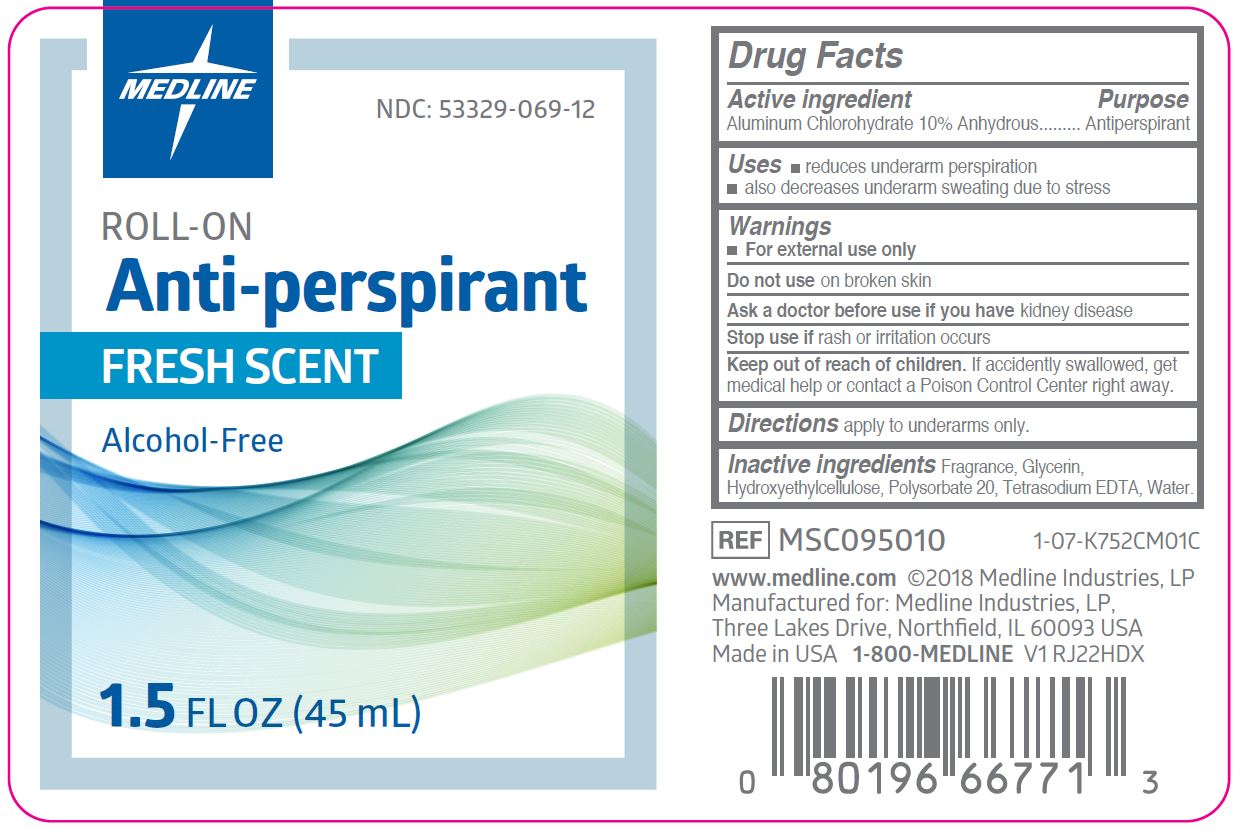 DRUG LABEL: Roll On Anti Perspirant
NDC: 53329-069 | Form: SOLUTION
Manufacturer: Medline Industries, LP
Category: otc | Type: HUMAN OTC DRUG LABEL
Date: 20241115

ACTIVE INGREDIENTS: ALUMINUM CHLOROHYDRATE 10 g/100 mL
INACTIVE INGREDIENTS: WATER; GLYCERIN; POLYSORBATE 20; HYDROXYETHYL CELLULOSE (2000 CPS AT 1%); EDETATE SODIUM

069 Roll-On Anti-Perspirant

Active ingredient

Aluminum Chlorohydrate 10% Anhydrous

Purpose

Antiperspirant

Uses

- reduces underarm perspiration
- also decreases underarm sweating due to stress

Warnings

For external use only.

Do not use

on broken skin

Ask a doctor before use if

you have kidney disease

Stop use if

rash or irritation occurs

Keep out of reach of children.

If swallowed, get medical help or contact a Poison Control Center right away.

Directions

apply to underarms only

Inactive ingredients

fragrance, gylcerin, hydroxyethylcellulose, polysorbate 20, tetrasodium EDTA, water

Manufacturing Information

Manufactured for: Medline Industries, LP

Three Lakes Drive, Northfield, IL 60093 USA

Made in USA

www.medline.com

1-800-MEDLINE

REF: MSC095010

V1 RJ22HDX